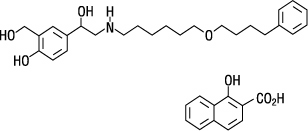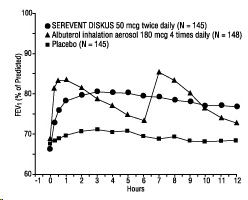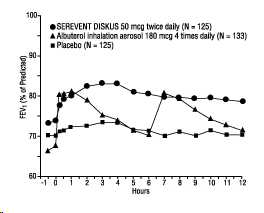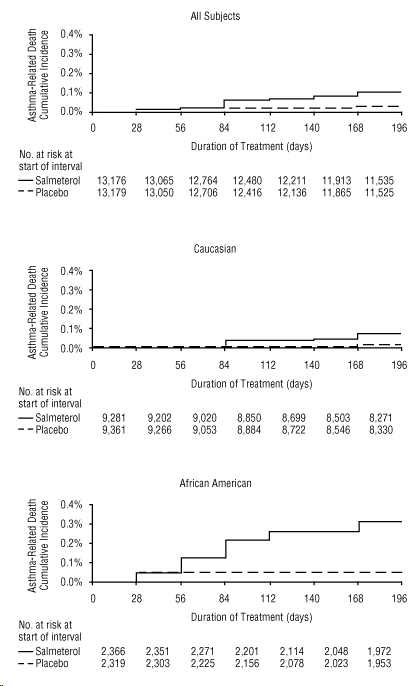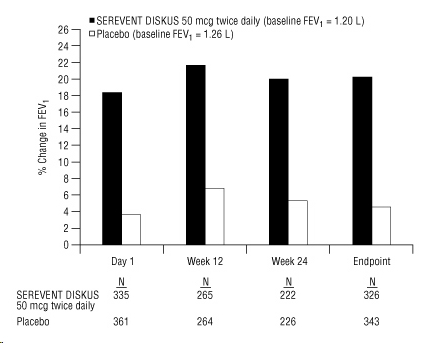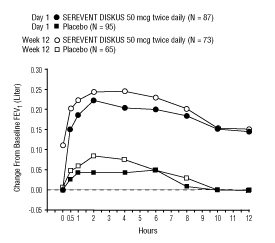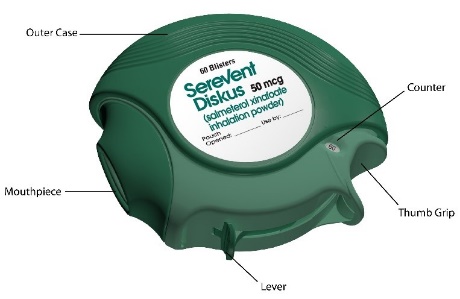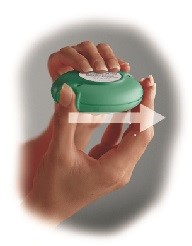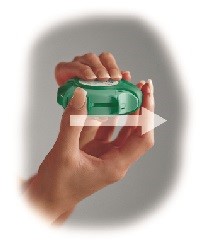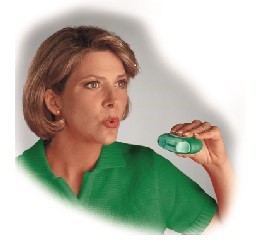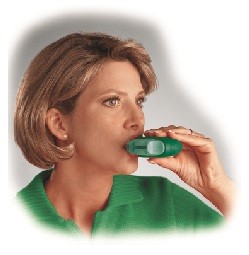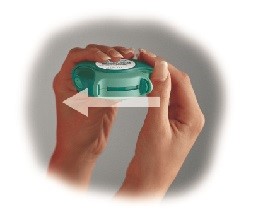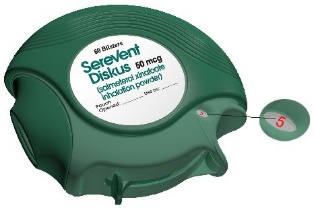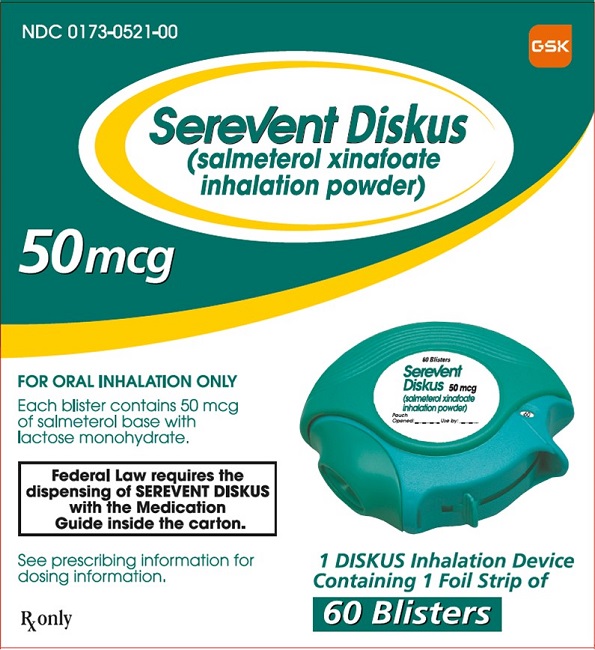 DRUG LABEL: SEREVENT
NDC: 0173-0521 | Form: POWDER, METERED
Manufacturer: GlaxoSmithKline LLC
Category: prescription | Type: HUMAN PRESCRIPTION DRUG LABEL
Date: 20221010

ACTIVE INGREDIENTS: SALMETEROL XINAFOATE 50 ug/1 1
INACTIVE INGREDIENTS: LACTOSE, UNSPECIFIED FORM

HIGHLIGHTS OF PRESCRIBING INFORMATION

These highlights do not include all the information needed to use SEREVENT DISKUS safely and effectively. See full prescribing information for SEREVENT DISKUS.
SEREVENT DISKUS (salmeterol xinafoate inhalation powder), for oral inhalation use
Initial U.S. Approval: 1994

WARNING: ASTHMA-RELATED DEATH

See full prescribing information for complete boxed warning.

- Long-acting beta2-adrenergic agonists (LABA), such as salmeterol, the active ingredient in SEREVENT DISKUS, as monotherapy (without inhaled corticosteroids [ICS]) increase the risk of asthma-related death. A U.S. trial showed an increase in asthma-related deaths in subjects receiving salmeterol (13 deaths out of 13,176 subjects treated for 28 weeks on salmeterol versus 3 out of 13,179 subjects on placebo). When LABA are used in fixed-dose combination with ICS, data from large clinical trials do not show a significant increase in the risk of serious asthma-related events (hospitalizations, intubations, death) compared with ICS alone. (5.1)
- Prescribe SEREVENT DISKUS only as additional therapy for patients with asthma who are currently taking but are inadequately controlled on an ICS. Do not use SEREVENT DISKUS for patients whose asthma is adequately controlled on low- or medium-dose ICS. (1.1, 5.1)
- Available data from controlled clinical trials suggest that LABA as monotherapy increase the risk of asthma-related hospitalization in pediatric and adolescent patients. (5.1)

1 INDICATIONS AND USAGE

SEREVENT DISKUS is a LABA indicated for:

- Treatment of asthma in patients aged 4 years and older with an ICS. (1.1)
- Prevention of exercise-induced bronchospasm (EIB) in patients aged 4 years and older. (1.2)
- Maintenance treatment of bronchospasm associated with chronic obstructive pulmonary disease (COPD). (1.3)

Important limitation of use: Not indicated for relief of acute bronchospasm. (1.1, 1.3)

2 DOSAGE AND ADMINISTRATION

- For oral inhalation only. (2)
- Treatment of asthma in patients aged 4 years and older: 1 inhalation twice daily in addition to concomitant treatment with an ICS. (2.1)
- EIB: 1 inhalation at least 30 minutes before exercise. (2.2)
- Maintenance treatment of bronchospasm associated with COPD: 1 inhalation twice daily. (2.3)

3 DOSAGE FORMS AND STRENGTHS

Inhalation powder: Inhaler containing salmeterol (50 mcg) as a powder formulation for oral inhalation. (3)

4 CONTRAINDICATIONS

- Asthma: Without concomitant use of an ICS. (4)
- Primary treatment of status asthmaticus or acute episodes of asthma or COPD requiring intensive measures. (4)
- Severe hypersensitivity to milk proteins or demonstrated hypersensitivity to salmeterol or any of the excipients. (4)

5 WARNINGS AND PRECAUTIONS

- LABA as monotherapy (without ICS) for asthma increase the risk of asthma-related death and asthma-related hospitalizations. Prescribe for asthma only as concomitant therapy with an inhaled corticosteroid. (5.1)
- Do not initiate in acutely deteriorating asthma or COPD. Do not use to treat acute symptoms. (5.2)
- Not a substitute for corticosteroids. Patients with asthma must take a concomitant ICS. (5.3)
- Do not use in combination with an additional medicine containing a LABA because of risk of overdose. (5.4)
- If paradoxical bronchospasm occurs, discontinue SEREVENT DISKUS and institute alternative therapy. (5.5)
- Use with caution in patients with cardiovascular or central nervous system disorders because of beta-adrenergic stimulation. (5.6)
- Use with caution in patients with convulsive disorders, thyrotoxicosis, diabetes mellitus, and ketoacidosis. (5.9)
- Be alert to hypokalemia and hyperglycemia. (5.10)

6 ADVERSE REACTIONS

Most common adverse reactions (incidence ≥5%) are:

- Asthma: Headache, influenza, nasal/sinus congestion, pharyngitis, rhinitis, tracheitis/bronchitis. (6.1)
- COPD: Cough, headache, musculoskeletal pain, throat irritation, viral respiratory infection. (6.2)

To report SUSPECTED ADVERSE REACTIONS, contact GlaxoSmithKline at 1-888-825-5249 or FDA at 1-800-FDA-1088 or www.fda.gov/medwatch

7 DRUG INTERACTIONS

- Strong cytochrome P450 3A4 inhibitors (e.g., ritonavir, ketoconazole): Use not recommended. May increase risk of cardiovascular effects. (7.1)
- Monoamine oxidase inhibitors and tricyclic antidepressants: Use with extreme caution. May potentiate effect of salmeterol on vascular system. (7.2)
- Beta-blockers: Use with caution. May block bronchodilatory effects of beta-agonists and produce severe bronchospasm. (7.3)
- Diuretics: Use with caution. Electrocardiographic changes and/or hypokalemia associated with non–potassium-sparing diuretics may worsen with concomitant beta-agonists. (7.4)

8 USE IN SPECIFIC POPULATIONS

Hepatic impairment: Monitor patients for signs of increased drug exposure. (8.6)

FULL PRESCRIBING INFORMATION

WARNING: ASTHMA-RELATED DEATH

Long-acting beta2-adrenergic agonists (LABA), such as salmeterol, the active ingredient in SEREVENT DISKUS, as monotherapy (without inhaled corticosteroids [ICS]) increase the risk of asthma-related death. Data from a large placebo-controlled U.S. trial that compared the safety of salmeterol with placebo added to usual asthma therapy showed an increase in asthma-related deaths in subjects receiving salmeterol (13 deaths out of 13,176 subjects treated for 28 weeks on salmeterol versus 3 deaths out of 13,179 subjects on placebo). Use of background ICS was not required in this study. When LABA are used in fixed-dose combination with ICS, data from large clinical trials do not show a significant increase in the risk of serious asthma-related events (hospitalizations, intubations, death) compared with ICS alone.

Use of SEREVENT DISKUS for the treatment of asthma as monotherapy without a concomitant ICS is contraindicated. Use SEREVENT DISKUS only as additional therapy for patients with asthma who are currently taking but are inadequately controlled on an ICS. Do not use SEREVENT DISKUS for patients whose asthma is adequately controlled on low- or medium-dose ICS.

Pediatric and Adolescent Patients

Available data from controlled clinical trials suggest that LABA as monotherapy increase the risk of asthma-related hospitalization in pediatric and adolescent patients. For pediatric and adolescent patients with asthma who require addition of a LABA to an ICS, a fixed-dose combination product containing both an ICS and a LABA should ordinarily be used to ensure adherence with both drugs. In cases where use of an ICS and a LABA is clinically indicated, appropriate steps must be taken to ensure adherence with both treatment components. If adherence cannot be assured, a fixed-dose combination product containing both an ICS and a LABA is recommended.

1 INDICATIONS AND USAGE

1.1 Treatment of Asthma

SEREVENT DISKUS is indicated for the treatment of asthma and in the prevention of bronchospasm only as concomitant therapy with an ICS in patients aged 4 years and older with reversible obstructive airway disease, including patients with symptoms of nocturnal asthma. LABA, such as salmeterol, the active ingredient in SEREVENT DISKUS, as monotherapy (without ICS) increase the risk of asthma-related death [see Warnings and Precautions (5.1)]. Use of SEREVENT DISKUS for the treatment of asthma without concomitant use of an ICS is contraindicated [see Contraindications (4)]. Use SEREVENT DISKUS only as additional therapy for patients with asthma who are currently taking but are inadequately controlled on an ICS. Do not use SEREVENT DISKUS for patients whose asthma is adequately controlled on low- or medium-dose ICS.

Pediatric and Adolescent Patients

Available data from controlled clinical trials suggest that LABA as monotherapy increase the risk of asthma-related hospitalization in pediatric and adolescent patients. For pediatric and adolescent patients with asthma who require addition of a LABA to an ICS, a fixed-dose combination product containing both an ICS and a LABA should ordinarily be used to ensure adherence with both drugs. In cases where use of a separate ICS and a LABA is clinically indicated, appropriate steps must be taken to ensure adherence with both treatment components. If adherence cannot be assured, a fixed-dose combination product containing both an ICS and a LABA is recommended.

Important Limitation of Use

SEREVENT DISKUS is NOT indicated for the relief of acute bronchospasm.

1.2 Prevention of Exercise-Induced Bronchospasm

SEREVENT DISKUS is also indicated for prevention of exercise-induced bronchospasm (EIB) in patients aged 4 years and older. Use of SEREVENT DISKUS as a single agent for the prevention of EIB may be clinically indicated in patients who do not have persistent asthma. In patients with persistent asthma, use of SEREVENT DISKUS for the prevention of EIB may be clinically indicated, but the treatment of asthma should include an ICS.

1.3 Maintenance Treatment of Chronic Obstructive Pulmonary Disease

SEREVENT DISKUS is indicated for the long-term twice-daily administration in the maintenance treatment of bronchospasm associated with chronic obstructive pulmonary disease (COPD) (including emphysema and chronic bronchitis).

Important Limitation of Use

SEREVENT DISKUS is NOT indicated for the relief of acute bronchospasm.

2 DOSAGE AND ADMINISTRATION

SEREVENT DISKUS should be administered by the orally inhaled route only.

More frequent administration or a greater number of inhalations (more than 1 inhalation twice daily) is not recommended as some patients are more likely to experience adverse effects. Patients using SEREVENT DISKUS should not use additional LABA for any reason. [See Warnings and Precautions (5.4, 5.6).]

2.1 Asthma

LABA, such as salmeterol, the active ingredient in SEREVENT DISKUS, as monotherapy (without ICS) increase the risk of asthma-related death [see Warnings and Precautions (5.1)].

Because of this risk, use of SEREVENT DISKUS for the treatment of asthma without concomitant use of an ICS is contraindicated. Use SEREVENT DISKUS only as additional therapy for patients with asthma who are currently taking but are inadequately controlled on an ICS. Do not use SEREVENT DISKUS for patients whose asthma is adequately controlled on low- or medium-dose ICS.

Pediatric and Adolescent Patients

Available data from controlled clinical trials suggest that LABA as monotherapy increase the risk of asthma-related hospitalization in pediatric and adolescent patients. For patients with asthma younger than 18 years who require addition of a LABA to an ICS, a fixed-dose combination product containing both an ICS and a LABA should ordinarily be used to ensure adherence with both drugs. In cases where use of a separate ICS and a LABA is clinically indicated, appropriate steps must be taken to ensure adherence with both treatment components. If adherence cannot be assured, a fixed-dose combination product containing both an ICS and a LABA is recommended.

For bronchodilatation and prevention of symptoms of asthma, including the symptoms of nocturnal asthma, the usual dosage for adults and children aged 4 years and older is 1 inhalation (50 mcg) twice daily, approximately 12 hours apart. If a previously effective dosage regimen fails to provide the usual response, medical advice should be sought immediately as this is often a sign of destabilization of asthma. Under these circumstances, the therapeutic regimen should be reevaluated. If symptoms arise in the period between doses, an inhaled, short-acting beta2-agonist should be taken for immediate relief.

2.2 Exercise-Induced Bronchospasm

Use of SEREVENT DISKUS as a single agent for the prevention of EIB may be clinically indicated in patients who do not have persistent asthma. In patients with persistent asthma, use of SEREVENT DISKUS for the prevention of EIB may be clinically indicated, but the treatment of asthma should include an ICS. One inhalation of SEREVENT DISKUS at least 30 minutes before exercise has been shown to protect patients against EIB. When used intermittently as needed for prevention of EIB, this protection may last up to 9 hours in adults and adolescents and up to 12 hours in patients aged 4 to 11 years. Additional doses of SEREVENT should not be used for 12 hours after the administration of this drug. Patients who are receiving SEREVENT DISKUS twice daily should not use additional SEREVENT for prevention of EIB.

2.3 Chronic Obstructive Pulmonary Disease

For maintenance treatment of bronchospasm associated with COPD (including chronic bronchitis and emphysema), the dosage for adults is 1 inhalation (50 mcg) twice daily, approximately 12 hours apart.

3 DOSAGE FORMS AND STRENGTHS

Inhalation powder: Inhaler containing a foil blister strip of powder formulation for oral inhalation. The strip contains salmeterol 50 mcg per blister.

4 CONTRAINDICATIONS

Use of SEREVENT DISKUS for the treatment of asthma without concomitant use of an ICS is contraindicated [see Warnings and Precautions (5.1)].

The use of SEREVENT DISKUS is contraindicated in the following conditions:

- Primary treatment of status asthmaticus or other acute episodes of asthma or COPD where intensive measures are required [see Warnings and Precautions (5.2)]
- Severe hypersensitivity to milk proteins or demonstrated hypersensitivity to salmeterol or any of the excipients [see Warnings and Precautions (5.7), Adverse Reactions (6.3), Description (11)]

5 WARNINGS AND PRECAUTIONS

5.1 Asthma-Related Death

LABA, such as salmeterol, the active ingredient in SEREVENT DISKUS, as monotherapy (without ICS) increase the risk of asthma-related death. When LABA are used in fixed-dose combination with ICS, data from large clinical trials do not show a significant increase in the risk of serious asthma-related events (hospitalizations, intubations, death) compared with ICS alone.

Use of SEREVENT DISKUS for the treatment of asthma without concomitant use of an ICS is contraindicated. Use SEREVENT DISKUS only as additional therapy for patients with asthma who are currently taking but are inadequately controlled on an ICS. Do not use SEREVENT DISKUS for patients whose asthma is adequately controlled on low- or medium-dose ICS.

Pediatric and Adolescent Patients

Available data from controlled clinical trials suggest that LABA as monotherapy increase the risk of asthma-related hospitalization in pediatric and adolescent patients. For pediatric and adolescent patients with asthma who require addition of a LABA to an ICS, a fixed-dose combination product containing both an ICS and a LABA should ordinarily be used to ensure adherence with both drugs. In cases where use of a separate ICS and a LABA is clinically indicated, appropriate steps must be taken to ensure adherence with both treatment components. If adherence cannot be assured, a fixed-dose combination product containing both an ICS and a LABA is recommended.

The Salmeterol Multicenter Asthma Research Trial (SMART) was a large 28-week placebo-controlled U.S. trial comparing the safety of salmeterol (SEREVENT Inhalation Aerosol) with placebo, each added to usual asthma therapy, that showed an increase in asthma-related deaths in subjects receiving salmeterol [see Clinical Studies (14.1)]. Given the similar basic mechanisms of action of beta2-agonists, the findings seen in the SMART trial are considered a class effect.

A 16-week clinical trial performed in the United Kingdom, the Salmeterol Nationwide Surveillance (SNS) trial, showed results similar to the SMART trial. In the SNS trial, the rate of asthma-related death was numerically, though not statistically significantly, greater in subjects with asthma treated with salmeterol (42 mcg twice daily) than those treated with albuterol (180 mcg 4 times daily) added to usual asthma therapy.

The SNS and SMART trials enrolled subjects with asthma. Available data do not suggest an increased risk of death with use of LABA in patients with COPD.

5.2 Deterioration of Disease and Acute Episodes

SEREVENT DISKUS should not be initiated in patients during rapidly deteriorating or potentially life-threatening episodes of asthma or COPD. SEREVENT DISKUS has not been studied in subjects with acutely deteriorating asthma or COPD. The initiation of SEREVENT DISKUS in this setting is not appropriate.

Serious acute respiratory events, including fatalities, have been reported when salmeterol has been initiated in patients with significantly worsening or acutely deteriorating asthma. In most cases, these have occurred in patients with severe asthma (e.g., patients with a history of corticosteroid dependence, low pulmonary function, intubation, mechanical ventilation, frequent hospitalizations, previous life-threatening acute asthma exacerbations) and in some patients with acutely deteriorating asthma (e.g., patients with significantly increasing symptoms; increasing need for inhaled, short-acting beta2-agonists; decreasing response to usual medications; increasing need for systemic corticosteroids; recent emergency room visits; deteriorating lung function). However, these events have occurred in a few patients with less severe asthma as well. It was not possible from these reports to determine whether salmeterol contributed to these events.

Increasing use of inhaled, short-acting beta2-agonists is a marker of deteriorating asthma. In this situation, the patient requires immediate reevaluation with reassessment of the treatment regimen, giving special consideration to the possible need for adding additional ICS or initiating systemic corticosteroids. Patients should not use more than 1 inhalation twice daily of SEREVENT DISKUS.

SEREVENT DISKUS should not be used for the relief of acute symptoms, i.e., as rescue therapy for the treatment of acute episodes of bronchospasm. An inhaled, short-acting beta2-agonist, not SEREVENT DISKUS, should be used to relieve acute symptoms such as shortness of breath. When prescribing SEREVENT DISKUS, the healthcare provider should also prescribe an inhaled, short-acting beta2-agonist (e.g., albuterol) for treatment of acute symptoms.

When beginning treatment with SEREVENT DISKUS, patients who have been taking oral or inhaled, short-acting beta2-agonists on a regular basis (e.g., 4 times a day) should be instructed to discontinue the regular use of these drugs.

5.3 SEREVENT DISKUS is Not a Substitute for Corticosteroids

There are no data demonstrating that SEREVENT DISKUS has a clinical anti-inflammatory effect such as that associated with corticosteroids. When initiating and throughout treatment with SEREVENT DISKUS in patients receiving oral or ICS for treatment of asthma, patients must continue taking a suitable dosage of corticosteroids to maintain clinical stability even if they feel better as a result of initiating SEREVENT DISKUS. Any change in corticosteroid dosage should be made ONLY after clinical evaluation.

5.4 Excessive Use of SEREVENT DISKUS and Use with Other Long-acting Beta2-agonists

SEREVENT DISKUS should not be used more often than recommended, at higher doses than recommended, or in conjunction with other medicines containing LABA, as an overdose may result. Clinically significant cardiovascular effects and fatalities have been reported in association with excessive use of inhaled sympathomimetic drugs. Patients using SEREVENT DISKUS should not use another medicine containing a LABA (e.g., formoterol fumarate, arformoterol tartrate, indacaterol) for any reason.

5.5 Paradoxical Bronchospasm and Upper Airway Symptoms

As with other inhaled medicines, SEREVENT DISKUS can produce paradoxical bronchospasm, which may be life threatening. If paradoxical bronchospasm occurs following dosing with SEREVENT DISKUS, it should be treated immediately with an inhaled, short-acting bronchodilator; SEREVENT DISKUS should be discontinued immediately; and alternative therapy should be instituted. Upper airway symptoms of laryngeal spasm, irritation, or swelling, such as stridor and choking, have been reported in patients receiving SEREVENT DISKUS.

5.6 Cardiovascular and Central Nervous System Effects

Excessive beta-adrenergic stimulation has been associated with seizures, angina, hypertension or hypotension, tachycardia with rates up to 200 beats/min, arrhythmias, nervousness, headache, tremor, palpitation, nausea, dizziness, fatigue, malaise, and insomnia [see Overdosage (10)]. Therefore, SEREVENT DISKUS, like all products containing sympathomimetic amines, should be used with caution in patients with cardiovascular disorders, especially coronary insufficiency, cardiac arrhythmias, and hypertension.

Salmeterol can produce a clinically significant cardiovascular effect in some patients as measured by pulse rate, blood pressure, and/or symptoms. Although such effects are uncommon after administration of salmeterol at recommended doses, if they occur, the drug may need to be discontinued. In addition, beta-agonists have been reported to produce electrocardiogram (ECG) changes, such as flattening of the T wave, prolongation of the QTc interval, and ST segment depression. The clinical significance of these findings is unknown. Large doses of inhaled or oral salmeterol (12 to 20 times the recommended dose) have been associated with clinically significant prolongation of the QTc interval, which has the potential for producing ventricular arrhythmias. Fatalities have been reported in association with excessive use of inhaled sympathomimetic drugs.

5.7 Immediate Hypersensitivity Reactions

Immediate hypersensitivity reactions (e.g., urticaria, angioedema, rash, bronchospasm, hypotension), including anaphylaxis, may occur after administration of SEREVENT DISKUS. There have been reports of anaphylactic reactions in patients with severe milk protein allergy after inhalation of powder products containing lactose; therefore, patients with severe milk protein allergy should not use SEREVENT DISKUS [see Contraindications (4)].

5.8 Drug Interactions with Strong Cytochrome P450 3A4 Inhibitors

The use of strong cytochrome P450 3A4 (CYP3A4) inhibitors (e.g., ritonavir, atazanavir, clarithromycin, indinavir, itraconazole, nefazodone, nelfinavir, saquinavir, ketoconazole, telithromycin) with SEREVENT DISKUS is not recommended because increased cardiovascular adverse effects may occur [see Drug Interactions (7.1), Clinical Pharmacology (12.3)].

5.9 Coexisting Conditions

SEREVENT DISKUS, like all medicines containing sympathomimetic amines, should be used with caution in patients with convulsive disorders or thyrotoxicosis and in those who are unusually responsive to sympathomimetic amines. Doses of the related beta2-adrenoceptor agonist albuterol, when administered intravenously, have been reported to aggravate preexisting diabetes mellitus and ketoacidosis.

5.10 Hypokalemia and Hyperglycemia

Beta-adrenergic agonist medicines may produce significant hypokalemia in some patients, possibly through intracellular shunting, which has the potential to produce adverse cardiovascular effects [see Clinical Pharmacology (12.2)]. The decrease in serum potassium is usually transient, not requiring supplementation. Clinically significant and dose-related changes in blood glucose and/or serum potassium were seen infrequently during clinical trials with SEREVENT DISKUS at recommended doses.

6 ADVERSE REACTIONS

LABA, including salmeterol, the active ingredient in SEREVENT DISKUS, as monotherapy (without ICS) increase the risk of asthma-related death. Data from a large 28-week placebo-controlled U.S. trial that compared the safety of salmeterol or placebo added to usual asthma therapy showed an increase in asthma-related deaths in subjects receiving salmeterol. Available data from controlled clinical trials suggest that LABA as monotherapy increase the risk of asthma-related hospitalization in pediatric and adolescent patients [see Warnings and Precautions (5.1), Clinical Studies (14.1)].

Because clinical trials are conducted under widely varying conditions, adverse reaction rates observed in the clinical trials of a drug cannot be directly compared with rates in the clinical trials of another drug and may not reflect the rates observed in practice.

6.1 Clinical Trials Experience in Asthma

Adult and Adolescent Subjects Aged 12 Years and Older

Two multicenter, 12-week, placebo-controlled clinical trials evaluated twice-daily doses of SEREVENT DISKUS in subjects aged 12 years and older with asthma. Table 1 reports the incidence of adverse reactions in these 2 trials.

Table 1. Adverse Reactions with SEREVENT DISKUS with ≥3% Incidence and More Common than Placebo in Adult and Adolescent Subjects with Asthmaa
Adverse Event | Percent of Subjects
Adverse Event | SEREVENT DISKUS; 50 mcg; Twice Daily; (n = 149) | Albuterol Inhalation Aerosol; 180 mcg; 4 Times Daily; (n = 150) | Placebo; (n = 152)
Ear, nose, and throat
Nasal/sinus congestion, pallor | 9 | 8 | 6
Rhinitis | 5 | 4 | 4
Neurological
Headache | 13 | 12 | 9
Respiratory
Asthma | 3 | <1 | 1
Tracheitis/bronchitis | 7 | 3 | 4
Influenza | 5 | 5 | 2
a Table 1 includes all events (whether considered drug-related or nondrug-related by the investigator) that occurred at a rate of ≥3% in the group receiving SEREVENT DISKUS and were more common than in the placebo group.

Pharyngitis, sinusitis, upper respiratory tract infection, and cough occurred at ≥3% but were more common in the placebo group. However, throat irritation has been described at rates exceeding that of placebo in other controlled clinical trials.

Additional Adverse Reactions: Other adverse reactions not previously listed, whether considered drug-related or not by the investigators, that were reported more frequently by subjects with asthma treated with SEREVENT DISKUS compared with subjects treated with placebo include the following: contact dermatitis, eczema, localized aches and pains, nausea, oral mucosal abnormality, pain in joint, paresthesia, pyrexia of unknown origin, sinus headache, and sleep disturbance.

Pediatric Subjects Aged 4 to 11 Years

Two multicenter, 12-week, controlled trials have evaluated twice-daily doses of SEREVENT DISKUS in subjects aged 4 to 11 years with asthma. Table 2 includes all events (whether considered drug-related or nondrug-related by the investigator) that occurred at a rate of ≥3% in the group receiving SEREVENT DISKUS and were more common than in the placebo group.

Table 2. Adverse Reaction Incidence in Two 12-Week Pediatric Clinical Trials in Subjects with Asthma
Adverse Event | Percent of Subjects
Adverse Event | SEREVENT DISKUS; 50 mcg; Twice Daily; (n = 211) | Albuterol Inhalation Aerosol; 200 mcg; 4 Times Daily; (n = 115) | Placebo; (n = 215)
Ear, nose, and throat
Ear signs and symptoms | 4 | 9 | 3
Pharyngitis | 6 | 3 | 3
Neurological
Headache | 17 | 20 | 14
Respiratory
Asthma | 4 | <1 | 2
Skin
Skin rashes | 4 | 2 | 3
Urticaria | 3 | 2 | 0

The following events were reported at an incidence of >1% in the salmeterol group and with a higher incidence than in the albuterol and placebo groups: gastrointestinal signs and symptoms, lower respiratory signs and symptoms, photodermatitis, and arthralgia and articular rheumatism.

In clinical trials evaluating concurrent therapy of salmeterol with ICS, adverse events were consistent with those previously reported for salmeterol, or with events that would be expected with the use of ICS.

Laboratory Test Abnormalities

Elevation of hepatic enzymes was reported in ≥1% of subjects in clinical trials. The elevations were transient and did not lead to discontinuation from the trials. In addition, there were no clinically relevant changes noted in glucose or potassium.

6.2 Clinical Trials Experience in Chronic Obstructive Pulmonary Disease

Two multicenter, 24-week, placebo-controlled U.S. trials evaluated twice-daily doses of SEREVENT DISKUS in subjects with COPD. For presentation (Table 3), the placebo data from a third trial, identical in design, subject entrance criteria, and overall conduct but comparing fluticasone propionate with placebo, were integrated with the placebo data from these 2 trials (total N = 341 for salmeterol and 576 for placebo).

Table 3. Adverse Reactions with SEREVENT DISKUS with ≥3% Incidence in U.S. Controlled Clinical Trials in Subjects with Chronic Obstructive Pulmonary Diseasea
Adverse Event | Percent of Subjects
Adverse Event | SEREVENT DISKUS; 50 mcg Twice Daily; (n = 341) | Placebo; (n = 576)
Cardiovascular
Hypertension | 4 | 2
Ear, nose, and throat
Throat irritation | 7 | 6
Nasal congestion/blockage | 4 | 3
Sinusitis | 4 | 2
Ear signs and symptoms | 3 | 1
Gastrointestinal
Nausea and vomiting | 3 | 3
Lower respiratory
Cough | 5 | 4
Rhinitis | 4 | 2
Viral respiratory infection | 5 | 4
Musculoskeletal
Musculoskeletal pain | 12 | 10
Muscle cramps and spasms | 3 | 1
Neurological
Headache | 14 | 11
Dizziness | 4 | 2
Average duration of exposure (days) | 138.5 | 128.9
a Table 3 includes all events (whether considered drug-related or nondrug-related by the investigator) that occurred at a rate of ≥3% in the group receiving SEREVENT DISKUS and were more common than in the placebo group.

Additional Adverse Reactions

Other adverse reactions occurring in the group receiving SEREVENT DISKUS that occurred at a frequency of ≥1% and were more common than in the placebo group were as follows: anxiety; arthralgia and articular rheumatism; bone and skeletal pain; candidiasis mouth/throat; dental discomfort and pain; dyspeptic symptoms; edema and swelling; gastrointestinal infections; hyperglycemia; hyposalivation; keratitis and conjunctivitis; lower respiratory signs and symptoms; migraines; muscle pain; muscle stiffness, tightness, and rigidity; musculoskeletal inflammation; pain; and skin rashes.

Adverse reactions to salmeterol are similar in nature to those seen with other selective beta2-adrenoceptor agonists, e.g., tachycardia; palpitations; immediate hypersensitivity reactions, including urticaria, angioedema, rash, bronchospasm; headache; tremor; nervousness; and paradoxical bronchospasm.

Laboratory Abnormalities

There were no clinically relevant changes in these trials. Specifically, no changes in potassium were noted.

6.3 Postmarketing Experience

In addition to adverse reactions reported from clinical trials, the following adverse reactions have been identified during postapproval use of salmeterol. Because these reactions are reported voluntarily from a population of uncertain size, it is not always possible to reliably estimate their frequency or establish a causal relationship to drug exposure. These events have been chosen for inclusion due to either their seriousness, frequency of reporting, or causal connection to salmeterol or a combination of these factors.

In extensive U.S. and worldwide postmarketing experience with salmeterol, serious exacerbations of asthma, including some that have been fatal, have been reported. In most cases, these have occurred in patients with severe asthma and/or in some patients in whom asthma has been acutely deteriorating [see Warnings and Precautions (5.2)], but they have also occurred in a few patients with less severe asthma. It was not possible from these reports to determine whether salmeterol contributed to these events.

Cardiovascular

Arrhythmias (including atrial fibrillation, supraventricular tachycardia, extrasystoles) and anaphylaxis.

Non-Site Specific

Very rare anaphylactic reaction in patients with severe milk protein allergy.

Respiratory

Reports of upper airway symptoms of laryngeal spasm, irritation, or swelling such as stridor or choking; oropharyngeal irritation.

7 DRUG INTERACTIONS

7.1 Inhibitors of Cytochrome P450 3A4

Salmeterol is a substrate of CYP3A4. The use of strong CYP3A4 inhibitors (e.g., ritonavir, atazanavir, clarithromycin, indinavir, itraconazole, nefazodone, nelfinavir, saquinavir, ketoconazole, telithromycin) with SEREVENT DISKUS is not recommended because increased cardiovascular adverse effects may occur.

In a drug interaction trial in 20 healthy subjects, coadministration of inhaled salmeterol (50 mcg twice daily) and oral ketoconazole (400 mg once daily) for 7 days resulted in greater systemic exposure to salmeterol (AUC increased 16-fold and Cmax increased 1.4-fold). Three (3) subjects were withdrawn due to beta2-agonist side effects (2 with prolonged QTc and 1 with palpitations and sinus tachycardia). Although there was no statistical effect on the mean QTc, coadministration of salmeterol and ketoconazole was associated with more frequent increases in QTc duration compared with salmeterol and placebo administration.

7.2 Monoamine Oxidase Inhibitors and Tricyclic Antidepressants

SEREVENT DISKUS should be administered with extreme caution to patients being treated with monoamine oxidase inhibitors or tricyclic antidepressants, or within 2 weeks of discontinuation of such agents, because the action of salmeterol on the vascular system may be potentiated by these agents.

7.3 Beta-adrenergic Receptor Blocking Agents

Beta-blockers not only block the pulmonary effect of beta-agonists, such as salmeterol, but may also produce severe bronchospasm in patients with asthma or COPD. Therefore, patients with asthma or COPD should not normally be treated with beta-blockers. However, under certain circumstances, there may be no acceptable alternatives to the use of beta-adrenergic blocking agents for these patients; cardioselective beta-blockers could be considered, although they should be administered with caution.

7.4 Non–Potassium-Sparing Diuretics

The ECG changes and/or hypokalemia that may result from the administration of non–potassium-sparing diuretics (such as loop or thiazide diuretics) can be acutely worsened by beta-agonists, especially when the recommended dose of the beta-agonist is exceeded. Although the clinical significance of these effects is not known, caution is advised in the coadministration of SEREVENT DISKUS with non–potassium-sparing diuretics.

8 USE IN SPECIFIC POPULATIONS

8.1 Pregnancy

Risk Summary

The available data from published epidemiological studies and case reports with use of SEREVENT DISKUS in pregnant women have not identified a drug-associated risk of major birth defects, miscarriage, or adverse maternal or fetal outcomes (see Data). Beta‑agonists may interfere with uterine contractility. There are clinical considerations in pregnant women with asthma (see Clinical Considerations).

Oral administration of salmeterol to pregnant rabbits caused teratogenicity characteristic of beta‑adrenoceptor stimulation at maternal doses approximately 50 times the maximum recommended human daily inhaled dose (MRHDID) on an AUC basis. These adverse effects generally occurred at large multiples of the MRHDID when salmeterol was administered by the oral route to achieve high systemic exposures. No such effects occurred at an oral salmeterol dose approximately 20 times the MRHDID (see Data).

The estimated background risk of major birth defects and miscarriage for the indicated population is unknown. All pregnancies have a background risk of birth defect, loss, or other adverse outcomes. In the U.S. general population, the estimated background risk of major birth defects and miscarriage in clinically recognized pregnancies is 2% to 4% and 15% to 20%, respectively.

Clinical Considerations

Disease-Associated Maternal and/or Embryofetal Risk: In women with poorly or moderately controlled asthma, there is an increased risk of pre-eclampsia in the mother and prematurity, low birth weight, and small for gestational age in the neonate. Severe asthma during pregnancy has been associated with maternal mortality, fetal mortality, or both. Pregnant women with asthma should be closely monitored and medication adjusted as necessary to maintain optimal asthma control.

Labor and Delivery: There are no adequate and well-controlled human studies that have evaluated the effects of SEREVENT DISKUS during labor and delivery. Because of the potential for beta-agonist interference with uterine contractility, use of SEREVENT DISKUS during labor should be restricted to those patients in whom the benefits clearly outweigh the risks.

Data

Human Data: While available studies cannot definitively establish the absence of risk, published data from epidemiological studies and case reports have not established an association with SEREVENT DISKUS use during pregnancy and major birth defects, miscarriage, or adverse maternal or fetal outcomes. The available studies have methodologic limitations, including retrospective data collection and inconsistent comparator groups.

Animal Data: In 3 embryofetal development studies, pregnant rabbits received oral administration of salmeterol at doses ranging from 100 to 10,000 mcg/kg/day during the period of organogenesis. In pregnant Dutch rabbits administered salmeterol doses approximately 50 times the MRHDID (on an AUC basis at maternal oral doses of 1,000 mcg/kg/day and higher), fetal toxic effects were observed characteristically resulting from beta‑adrenoceptor stimulation. These included precocious eyelid openings, cleft palate, sternebral fusion, limb and paw flexures, and delayed ossification of the frontal cranial bones. No such effects occurred at a salmeterol dose approximately 20 times the MRHDID (on an AUC basis at a maternal oral dose of 600 mcg/kg/day). New Zealand White rabbits were less sensitive since only delayed ossification of the frontal cranial bones was seen at a salmeterol dose approximately 2,000 times the MRHDID (on a mcg/m^2 basis at a maternal oral dose of 10,000 mcg/kg/day).

In 2 embryofetal development studies, pregnant rats received salmeterol by oral administration at doses ranging from 100 to 10,000 mcg/kg/day during the period of organogenesis. Salmeterol produced no maternal toxicity or embryofetal effects at doses up to 973 times the MRHDID (on a mcg/m^2 basis at maternal oral doses up to 10,000 mcg/kg/day).

In a peri- and post-natal development study in pregnant rats dosed by the oral route from late gestation through delivery and lactation, salmeterol at a dose 973 times the MRHDID (on a mcg/m^2 basis with a maternal oral dose of 10,000 mcg/kg/day) was fetotoxic and decreased the fertility of survivors.

Salmeterol xinafoate crossed the placenta following oral administration to mice and rats.

8.2 Lactation

Risk Summary

There is no information regarding the presence of salmeterol in human milk, the effects on the breastfed child, or the effects on milk production. Salmeterol is detected in rat milk (see Data). Salmeterol concentrations in human plasma after inhaled therapeutic doses are low and therefore concentrations in human breast milk are likely to be low [see Clinical Pharmacology (12.3)]. The developmental and health benefits of breastfeeding should be considered along with the mother’s clinical need for SEREVENT DISKUS and any potential adverse effects on the breastfed child from SEREVENT DISKUS or from the underlying maternal condition.

Data

Animal Data: Oral administration of salmeterol at a dose of 10,000 mcg/kg/day to lactating rats resulted in measurable levels in milk.

8.4 Pediatric Use

Available data from controlled clinical trials suggest that LABA used as monotherapy increase the risk of asthma-related hospitalization in pediatric and adolescent patients. For pediatric and adolescent patients with asthma who require addition of a LABA to an ICS, a fixed-dose combination product containing both an ICS and a LABA should ordinarily be used to ensure adherence with both drugs [see Indications and Usage (1.1), Warnings and Precautions (5.1)].

The safety and efficacy of SEREVENT DISKUS in adolescents (aged 12 years and older) have been established based on adequate and well-controlled trials conducted in adults and adolescents [see Clinical Studies (14.1)]. A large 28-week placebo-controlled U.S. trial comparing salmeterol (SEREVENT Inhalation Aerosol) and placebo, each added to usual asthma therapy, showed an increase in asthma-related deaths in subjects receiving salmeterol [see Clinical Studies (14.1)]. Post hoc analyses in pediatric subjects aged 12 to 18 years were also performed. Pediatric subjects accounted for approximately 12% of subjects in each treatment arm. Respiratory-related death or life-threatening experience occurred at a similar rate in the salmeterol group (0.12% [2/1,653]) and the placebo group (0.12% [2/1,622]; relative risk: 1.0 [95% CI: 0.1, 7.2]). All-cause hospitalization, however, was increased in the salmeterol group (2% [35/1,653]) versus the placebo group (less than 1% [16/1,622]; relative risk: 2.1 [95% CI: 1.1, 3.7]).

The safety and efficacy of SEREVENT DISKUS have been evaluated in over 2,500 subjects aged 4 to 11 years with asthma, 346 of whom were administered SEREVENT DISKUS for 1 year. Based on available data, no adjustment of dosage of SEREVENT DISKUS in pediatric patients is warranted for either asthma or EIB.

In 2 randomized, double-blind, controlled clinical trials of 12 weeks’ duration, SEREVENT DISKUS 50 mcg was administered to 211 pediatric subjects with asthma who did and who did not receive concurrent ICS. The efficacy of SEREVENT DISKUS was demonstrated over the 12-week treatment period with respect to peak expiratory flow (PEF) and forced expiratory volume in 1 second (FEV1). SEREVENT DISKUS was effective in demographic subgroups (gender and age) of the population.

In 2 randomized trials in children aged 4 to 11 years with asthma and EIB, a single 50-mcg dose of SEREVENT DISKUS prevented EIB when dosed 30 minutes prior to exercise, with protection lasting up to 11.5 hours in repeat testing following this single dose in many subjects.

8.5 Geriatric Use

Of the total number of adult and adolescent subjects with asthma who received SEREVENT DISKUS in chronic dosing clinical trials, 209 were aged 65 years and older. Of the total number of subjects with COPD who received SEREVENT DISKUS in chronic dosing clinical trials, 167 were aged 65 years and older and 45 were aged 75 years and older. No apparent differences in the safety of SEREVENT DISKUS were observed when geriatric subjects were compared with younger subjects in clinical trials. As with other beta2-agonists, however, special caution should be observed when using SEREVENT DISKUS in geriatric patients who have concomitant cardiovascular disease that could be adversely affected by beta-agonists. Data from the trials in subjects with COPD suggested a greater effect on FEV1 of SEREVENT DISKUS in subjects younger than 65 years, as compared with subjects aged 65 years and older. However, based on available data, no adjustment of dosage of SEREVENT DISKUS in geriatric patients is warranted.

8.6 Hepatic Impairment

Formal pharmacokinetic studies using SEREVENT DISKUS have not been conducted in patients with hepatic impairment. Since salmeterol is predominantly cleared by hepatic metabolism, impairment of liver function may lead to accumulation of salmeterol in plasma. Therefore, patients with hepatic disease should be closely monitored.

10 OVERDOSAGE

The expected signs and symptoms with overdosage of SEREVENT DISKUS are those of excessive beta-adrenergic stimulation and/or occurrence or exaggeration of any of the signs and symptoms of beta-adrenergic stimulation (e.g., seizures, angina, hypertension or hypotension, tachycardia with rates up to 200 beats/min, arrhythmias, nervousness, headache, tremor, muscle cramps, dry mouth, palpitation, nausea, dizziness, fatigue, malaise, insomnia, hyperglycemia, hypokalemia, metabolic acidosis). Overdosage with SEREVENT DISKUS can lead to clinically significant prolongation of the QTc interval, which can produce ventricular arrhythmias.

As with all inhaled sympathomimetic medicines, cardiac arrest and even death may be associated with an overdose of SEREVENT DISKUS.

Treatment consists of discontinuation of SEREVENT DISKUS together with appropriate symptomatic therapy. The judicious use of a cardioselective beta-receptor blocker may be considered, bearing in mind that such medication can produce bronchospasm. There is insufficient evidence to determine if dialysis is beneficial for overdosage of SEREVENT DISKUS. Cardiac monitoring is recommended in cases of overdosage.

11 DESCRIPTION

The active component of SEREVENT DISKUS is salmeterol xinafoate, a beta2-adrenergic bronchodilator. Salmeterol xinafoate is the racemic form of the 1-hydroxy-2-naphthoic acid salt of salmeterol. It has the chemical name 4-hydroxy-α^1-[[[6-(4-phenylbutoxy)hexyl]amino]methyl]-1,3-benzenedimethanol, 1-hydroxy-2-naphthalenecarboxylate and the following chemical structure:

Salmeterol xinafoate is a white powder with a molecular weight of 603.8, and the empirical formula is C25H37NO4•C11H8O3. It is freely soluble in methanol; slightly soluble in ethanol, chloroform, and isopropanol; and sparingly soluble in water.

SEREVENT DISKUS is a teal green plastic inhaler containing a foil blister strip. Each blister on the strip contains a white powder mix of micronized salmeterol xinafoate salt (72.5 mcg, equivalent to 50 mcg of salmeterol base) in 12.5 mg of formulation containing lactose monohydrate (which contains milk proteins). After the inhaler is activated, the powder is dispersed into the airstream created by the patient inhaling through the mouthpiece.

Under standardized in vitro test conditions, SEREVENT DISKUS delivers 47 mcg of salmeterol base per blister when tested at a flow rate of 60 L/min for 2 seconds.

In adult subjects with obstructive lung disease and severely compromised lung function (mean FEV1 20% to 30% of predicted), mean peak inspiratory flow (PIF) through the DISKUS inhaler was 82.4 L/min (range: 46.1 to 115.3 L/min).

The actual amount of drug delivered to the lung will depend on patient factors, such as inspiratory flow profile.

12 CLINICAL PHARMACOLOGY

12.1 Mechanism of Action

Salmeterol is a selective LABA. In vitro studies show salmeterol to be at least 50 times more selective for beta2-adrenoceptors than albuterol. Although beta2-adrenoceptors are the predominant adrenergic receptors in bronchial smooth muscle and beta1-adrenoceptors are the predominant receptors in the heart, there are also beta2-adrenoceptors in the human heart comprising 10% to 50% of the total beta-adrenoceptors. The precise function of these receptors has not been established, but their presence raises the possibility that even selective beta2-agonists may have cardiac effects.

The pharmacologic effects of beta2-adrenoceptor agonist drugs, including salmeterol, are at least in part attributable to stimulation of intracellular adenyl cyclase, the enzyme that catalyzes the conversion of adenosine triphosphate (ATP) to cyclic-3′,5′-adenosine monophosphate (cyclic AMP). Increased cyclic AMP levels cause relaxation of bronchial smooth muscle and inhibition of release of mediators of immediate hypersensitivity from cells, especially from mast cells.

In vitro tests show that salmeterol is a potent and long-lasting inhibitor of the release of mast cell mediators, such as histamine, leukotrienes, and prostaglandin D2, from human lung. Salmeterol inhibits histamine-induced plasma protein extravasation and inhibits platelet-activating factor–induced eosinophil accumulation in the lungs of guinea pigs when administered by the inhaled route. In humans, single doses of salmeterol administered via inhalation aerosol attenuate allergen-induced bronchial hyper-responsiveness.

12.2 Pharmacodynamics

Inhaled salmeterol, like other beta-adrenergic agonist drugs, can produce dose-related cardiovascular effects and effects on blood glucose and/or serum potassium [see Warnings and Precautions (5.6, 5.10)]. The cardiovascular effects (heart rate, blood pressure) associated with salmeterol inhalation aerosol occur with similar frequency, and are of similar type and severity, as those noted following albuterol administration.

The effects of rising inhaled doses of salmeterol and standard inhaled doses of albuterol were studied in volunteers and in subjects with asthma. Salmeterol doses up to 84 mcg administered as inhalation aerosol resulted in heart rate increases of 3 to 16 beats/min, about the same as albuterol dosed at 180 mcg by inhalation aerosol (4 to 10 beats/min). Adult and adolescent subjects receiving 50-mcg doses of salmeterol inhalation powder (n = 60) underwent continuous electrocardiographic monitoring during two 12-hour periods after the first dose and after 1 month of therapy, and no clinically significant dysrhythmias were noted. Also, pediatric patients receiving 50-mcg doses of salmeterol inhalation powder (n = 67) underwent continuous electrocardiographic monitoring during two 12-hour periods after the first dose and after 3 months of therapy, and no clinically significant dysrhythmias were noted.

In 24-week clinical studies in patients with COPD, the incidence of clinically significant abnormalities on the predose ECGs at Weeks 12 and 24 in patients who received salmeterol 50 mcg was not different compared with placebo.

No effect of treatment with salmeterol 50 mcg was observed on pulse rate and systolic and diastolic blood pressure in a subset of patients with COPD who underwent 12-hour serial vital sign measurements after the first dose (n = 91) and after 12 weeks of therapy (n = 74). Median changes from baseline in pulse rate and systolic and diastolic blood pressure were similar for patients receiving either salmeterol or placebo [see Adverse Reactions (6.1)].

Concomitant Use of SEREVENT DISKUS with Other Respiratory Medications

Short-acting Beta2-agonists: In two 12-week repetitive-dose clinical trials in adult and adolescent subjects with asthma (N = 149), the mean daily need for additional beta2-agonist in subjects using SEREVENT DISKUS was approximately 1½ inhalations/day. Twenty-six percent (26%) of the subjects in these trials used between 8 and 24 inhalations of short-acting beta-agonist per day on 1 or more occasions. Nine percent (9%) of the subjects in these trials averaged over 4 inhalations/day over the course of the 12-week trials. No increase in frequency of cardiovascular events was observed among the 3 subjects who averaged 8 to 11 inhalations/day; however, the safety of concomitant use of more than 8 inhalations/day of short-acting beta2-agonist with SEREVENT DISKUS has not been established. In 29 subjects who experienced worsening of asthma while receiving SEREVENT DISKUS during these trials, albuterol therapy administered via either nebulizer or inhalation aerosol (1 dose in most cases) led to improvement in FEV1 and no increase in occurrence of cardiovascular adverse events.

In 2 clinical trials in subjects with COPD, the mean daily need for additional beta2-agonist for subjects using SEREVENT DISKUS was approximately 4 inhalations/day. Twenty-four percent (24%) of subjects using SEREVENT DISKUS averaged 6 or more inhalations of albuterol per day over the course of the 24-week trials. No increase in frequency of cardiovascular adverse reactions was observed among subjects who averaged 6 or more inhalations per day.

Methylxanthines: The concurrent use of intravenously or orally administered methylxanthines (e.g., aminophylline, theophylline) by subjects receiving salmeterol has not been completely evaluated. In 1 clinical trial in subjects with asthma, 87 subjects receiving SEREVENT Inhalation Aerosol 42 mcg twice daily concurrently with a theophylline product had adverse event rates similar to those in 71 subjects receiving SEREVENT Inhalation Aerosol without theophylline. Resting heart rates were slightly higher in the subjects on theophylline but were little affected by therapy with SEREVENT Inhalation Aerosol.

In 2 clinical trials in subjects with COPD, 39 subjects receiving SEREVENT DISKUS concurrently with a theophylline product had adverse event rates similar to those in 302 subjects receiving SEREVENT DISKUS without theophylline. Based on the available data, the concomitant administration of methylxanthines with SEREVENT DISKUS did not alter the observed adverse event profile.

Cromoglycate: In clinical trials, inhaled cromolyn sodium did not alter the safety profile of salmeterol when administered concurrently.

12.3 Pharmacokinetics

Salmeterol xinafoate, an ionic salt, dissociates in solution so that the salmeterol and 1-hydroxy-2-naphthoic acid (xinafoate) moieties are absorbed, distributed, metabolized, and eliminated independently. Salmeterol acts locally in the lung; therefore, plasma levels do not predict therapeutic effect.

Absorption

Because of the small therapeutic dose, systemic levels of salmeterol are low or undetectable after inhalation of recommended doses (50 mcg of salmeterol inhalation powder twice daily). Following chronic administration of an inhaled dose of 50 mcg of salmeterol inhalation powder twice daily, salmeterol was detected in plasma within 5 to 45 minutes in 7 subjects with asthma; plasma concentrations were very low, with mean peak concentrations of 167 pg/mL at 20 minutes and no accumulation with repeated doses.

Distribution

The percentage of salmeterol bound to human plasma proteins averages 96% in vitro over the concentration range of 8 to 7,722 ng of salmeterol base per milliliter, much higher concentrations than those achieved following therapeutic doses of salmeterol.

Metabolism

Salmeterol base is extensively metabolized by hydroxylation, with subsequent elimination predominantly in the feces. No significant amount of unchanged salmeterol base was detected in either urine or feces.

An in vitro study using human liver microsomes showed that salmeterol is extensively metabolized to α-hydroxysalmeterol (aliphatic oxidation) by CYP3A4. Ketoconazole, a strong inhibitor of CYP3A4, essentially completely inhibited the formation of α-hydroxysalmeterol in vitro.

Elimination

In 2 healthy adult subjects who received 1 mg of radiolabeled salmeterol (as salmeterol xinafoate) orally, approximately 25% and 60% of the radiolabeled salmeterol was eliminated in urine and feces, respectively, over a period of 7 days. The terminal elimination half-life was about 5.5 hours (1 volunteer only).

The xinafoate moiety has no apparent pharmacologic activity. The xinafoate moiety is highly protein bound (>99%) and has a long elimination half-life of 11 days.

Drug Interaction Studies

Inhibitors of Cytochrome P450 3A4: Ketoconazole: In a placebo-controlled crossover drug interaction trial in 20 healthy male and female subjects, coadministration of salmeterol (50 mcg twice daily) and the strong CYP3A4 inhibitor ketoconazole (400 mg once daily) for 7 days resulted in a significant increase in plasma salmeterol exposure as determined by a 16-fold increase in AUC (ratio with and without ketoconazole 15.76 [90% CI: 10.66, 23.31]) mainly due to increased bioavailability of the swallowed portion of the dose. Peak plasma salmeterol concentrations were increased by 1.4-fold (90% CI: 1.23, 1.68). Three (3) out of 20 subjects (15%) were withdrawn from salmeterol and ketoconazole coadministration due to beta-agonist–mediated systemic effects (2 with QTc prolongation and 1 with palpitations and sinus tachycardia). Coadministration of salmeterol and ketoconazole did not result in a clinically significant effect on mean heart rate, mean blood potassium, or mean blood glucose. Although there was no statistical effect on the mean QTc, coadministration of salmeterol and ketoconazole was associated with more frequent increases in QTc duration compared with salmeterol and placebo administration.

Erythromycin: In a repeat-dose trial in 13 healthy subjects, concomitant administration of erythromycin (a moderate CYP3A4 inhibitor) and salmeterol inhalation aerosol resulted in a 40% increase in salmeterol Cmax at steady state (ratio with and without erythromycin 1.4 [90% CI: 0.96, 2.03], P = 0.12), a 3.6-beat/min increase in heart rate ([95% CI: 0.19, 7.03], P<0.04), a 5.8-msec increase in QTc interval ([95% CI: -6.14, 17.77], P = 0.34), and no change in plasma potassium.

13 NONCLINICAL TOXICOLOGY

13.1 Carcinogenesis, Mutagenesis, Impairment of Fertility

In an 18-month carcinogenicity study in CD-mice, salmeterol at oral doses of 1,400 mcg/kg and above (approximately 20 times the MRHDID for adults and children based on comparison of the plasma AUCs) caused a dose-related increase in the incidence of smooth muscle hyperplasia, cystic glandular hyperplasia, leiomyomas of the uterus, and ovarian cysts. No tumors were seen at 200 mcg/kg (approximately 3 times the MRHDID for adults and children based on comparison of the AUCs).

In a 24-month oral and inhalation carcinogenicity study in Sprague Dawley rats, salmeterol caused a dose-related increase in the incidence of mesovarian leiomyomas and ovarian cysts at doses of 680 mcg/kg and above (approximately 66 and 35 times the MRHDID for adults and children, respectively, on a mcg/m^2 basis). No tumors were seen at 210 mcg/kg (approximately 20 and 10 times the MRHDID for adults and children, respectively, on a mcg/m^2 basis). These findings in rodents are similar to those reported previously for other beta-adrenergic agonist drugs. The relevance of these findings to human use is unknown.

Salmeterol produced no detectable or reproducible increases in microbial and mammalian gene mutation in vitro. No clastogenic activity occurred in vitro in human lymphocytes or in vivo in a rat micronucleus test.

Fertility and reproductive performance were unaffected in male and female rats at oral doses up to 2,000 mcg/kg (approximately 195 times the MRHDID for adults on a mcg/m^2 basis).

13.2 Animal Toxicology and/or Pharmacology

Preclinical

Studies in laboratory animals (minipigs, rodents, and dogs) have demonstrated the occurrence of cardiac arrhythmias and sudden death (with histologic evidence of myocardial necrosis) when beta-agonists and methylxanthines are administered concurrently. The clinical relevance of these findings is unknown.

14 CLINICAL STUDIES

14.1 Asthma

The initial trials supporting the approval of SEREVENT DISKUS for the treatment of asthma did not require the regular use of ICS. However, for the treatment of asthma, SEREVENT DISKUS is currently indicated only as concomitant therapy with an ICS [see Indications and Usage (1.1)].

Adult and Adolescent Subjects Aged 12 Years and Older

In 2 randomized double-blind trials, SEREVENT DISKUS was compared with albuterol inhalation aerosol and placebo in adolescent and adult subjects with mild-to-moderate asthma (protocol defined as 50% to 80% predicted FEV1, actual mean of 67.7% at baseline), including subjects who did and who did not receive concurrent ICS. The efficacy of SEREVENT DISKUS was demonstrated over the 12-week period with no change in effectiveness over this time period (Figure 1). There were no gender- or age-related differences in safety or efficacy. No development of tachyphylaxis to the bronchodilator effect was noted in these trials. FEV1 measurements (mean change from baseline) from these two 12-week trials are shown in Figure 1 for both the first and last treatment days.

Figure 1. Serial 12-Hour FEV1 from Two 12-Week Clinical Trials in Subjects with Asthma

First Treatment Day

Last Treatment Day (Week 12)

Table 4 shows the treatment effects seen during daily treatment with SEREVENT DISKUS for 12 weeks in adolescent and adult subjects with mild-to-moderate asthma.

Table 4. Daily Efficacy Measurements in Two 12-Week Clinical Trials (Combined Data)
Parameter | Time | SEREVENT DISKUS | Albuterol Inhalation Aerosol | Placebo
No. of randomized subjects |  | 149 | 148 | 152
Mean AM peak expiratory flow (L/min) | Baseline 12 weeks | 395 | 394 | 394
Mean AM peak expiratory flow (L/min) | Baseline 12 weeks | 427a | 394 | 396
Mean % days with no asthma symptoms | Baseline 12 weeks | 13 | 12 | 14
Mean % days with no asthma symptoms | Baseline 12 weeks | 33 | 21 | 20
Mean % nights with no awakenings | Baseline 12 weeks | 63 | 68 | 70
Mean % nights with no awakenings | Baseline 12 weeks | 85a | 71 | 73
Rescue medications (mean no. of inhalations per day) | Baseline 12 weeks | 4.3 | 4.3 | 4.2
Rescue medications (mean no. of inhalations per day) | Baseline 12 weeks | 1.6b | 2.2 | 3.3
Asthma exacerbations (%) |  | 15 | 16 | 14
a Statistically superior to placebo and albuterol (P<0.001).
b Statistically superior to placebo (P<0.001).

Maintenance of efficacy for periods up to 1 year has been documented.

SEREVENT DISKUS and SEREVENT Inhalation Aerosol were compared with placebo in 2 additional randomized double-blind clinical trials in adolescent and adult subjects with mild-to-moderate asthma. SEREVENT DISKUS 50 mcg and SEREVENT Inhalation Aerosol 42 mcg, both administered twice daily, produced significant improvements in pulmonary function compared with placebo over the 12-week period. While no statistically significant differences were observed between the active treatments for any of the efficacy assessments or safety evaluations performed, there were some efficacy measures on which the metered-dose inhaler appeared to provide better results. Similar findings were noted in 2 randomized, single-dose, crossover comparisons of SEREVENT DISKUS and SEREVENT Inhalation Aerosol for the prevention of EIB. Therefore, while SEREVENT DISKUS was comparable to SEREVENT Inhalation Aerosol in clinical trials in mild-to-moderate subjects with asthma, it should not be assumed that they will produce clinically equivalent outcomes in all subjects.

Subjects on Concomitant Inhaled Corticosteroids: In 4 clinical trials in adult and adolescent subjects with asthma (N = 1,922), the effect of adding SEREVENT Inhalation Aerosol to ICS therapy was evaluated over a 24-week treatment period. The trials compared the addition of salmeterol therapy to an increase (at least doubling) of the ICS dose.

Two randomized, double-blind, controlled, parallel-group clinical trials (N = 997) enrolled subjects (aged 18 to 82 years) with persistent asthma who were previously maintained but not adequately controlled on ICS therapy. During the 2-week run-in period, all subjects were switched to beclomethasone dipropionate (BDP) 168 mcg twice daily. Subjects still not adequately controlled were randomized to either the addition of SEREVENT Inhalation Aerosol 42 mcg twice daily or an increase of BDP to 336 mcg twice daily. As compared with the doubled dose of BDP, the addition of SEREVENT Inhalation Aerosol resulted in statistically significantly greater improvements in pulmonary function and asthma symptoms, and statistically significantly greater reduction in supplemental albuterol use. The percent of subjects who experienced asthma exacerbations overall was not different between groups (i.e., 16.2% in the group receiving SEREVENT Inhalation Aerosol versus 17.9% in the higher-dose beclomethasone dipropionate group).

Two randomized, double-blind, controlled, parallel-group clinical trials (N = 925) enrolled subjects (aged 12 to 78 years) with persistent asthma who were previously maintained but not adequately controlled on prior asthma therapy. During the 2- to 4-week run-in period, all subjects were switched to fluticasone propionate 88 mcg twice daily. Subjects still not adequately controlled were randomized to either the addition of SEREVENT Inhalation Aerosol 42 mcg twice daily or an increase of fluticasone propionate to 220 mcg twice daily. As compared with the increased (2.5 times) dose of fluticasone propionate, the addition of SEREVENT Inhalation Aerosol resulted in statistically significantly greater improvements in pulmonary function and asthma symptoms, and statistically significantly greater reductions in supplemental albuterol use. Fewer subjects receiving SEREVENT Inhalation Aerosol experienced asthma exacerbations than those receiving the higher dose of fluticasone propionate (8.8% versus 13.8%).

Table 5 shows the treatment effects seen during daily treatment with SEREVENT Inhalation Aerosol for 24 weeks in adolescent and adult subjects with mild-to-moderate asthma.

Onset of Action: During the initial treatment day in several multiple-dose clinical trials with SEREVENT DISKUS in subjects with asthma, the median time to onset of clinically significant bronchodilatation (≥15% improvement in FEV1) ranged from 30 to 48 minutes after a 50-mcg dose.

One hour after a single dose of 50 mcg of SEREVENT DISKUS, the majority of subjects had ≥15% improvement in FEV1. Maximum improvement in FEV1 generally occurred within 180 minutes, and clinically significant improvement continued for 12 hours in most subjects.

Pediatric Subjects

In a randomized, double-blind, controlled trial (N = 449), 50 mcg of SEREVENT DISKUS was administered twice daily to pediatric subjects with asthma who did and who did not receive concurrent ICS. The efficacy of salmeterol inhalation powder was demonstrated over the 12-week treatment period with respect to periodic serial PEF (36% to 39% postdose increase from baseline) and FEV1 (32% to 33% postdose increase from baseline). Salmeterol was effective in demographic subgroup analyses (gender and age) and was effective when coadministered with other inhaled asthma medications such as short-acting bronchodilators and ICS. A second randomized, double-blind, placebo-controlled trial (N = 207) with 50 mcg of salmeterol inhalation powder via an alternate device supported the findings of the trial with the DISKUS.

Salmeterol Multicenter Asthma Research Trial

The SMART trial was a randomized double-blind trial that enrolled LABA-naive subjects with asthma (average age of 39 years; 71% Caucasian, 18% African American, 8% Hispanic) to assess the safety of salmeterol (SEREVENT Inhalation Aerosol) 42 mcg twice daily over 28 weeks compared with placebo when added to usual asthma therapy.

A planned interim analysis was conducted when approximately half of the intended number of subjects had been enrolled (N = 26,355), which led to premature termination of the trial. The results of the interim analysis showed that subjects receiving salmeterol were at increased risk for fatal asthma events (Table 5 and Figure 2). In the total population, a higher rate of asthma-related death occurred in subjects treated with salmeterol than those treated with placebo (0.10% versus 0.02%, relative risk: 4.37 [95% CI: 1.25, 15.34]).

Post hoc subpopulation analyses were performed. In Caucasians, asthma-related death occurred at a higher rate in subjects treated with salmeterol than in subjects treated with placebo (0.07% versus 0.01%, relative risk: 5.82 [95% CI: 0.70, 48.37]). In African Americans also, asthma-related death occurred at a higher rate in subjects treated with salmeterol than those treated with placebo (0.31% versus 0.04%, relative risk: 7.26 [95% CI: 0.89, 58.94]). Although the relative risks of asthma-related death were similar in Caucasians and African Americans, the estimate of excess deaths in subjects treated with salmeterol was greater in African Americans because there was a higher overall rate of asthma-related death in African American subjects (Table 5).

Post hoc analyses in pediatric subjects aged 12 to 18 years were also performed. Pediatric subjects accounted for approximately 12% of subjects in each treatment arm. Respiratory-related death or life-threatening experience occurred at a similar rate in the salmeterol group (0.12% [2/1,653]) and the placebo group (0.12% [2/1,622]; relative risk: 1.0 [95% CI: 0.1, 7.2]). All-cause hospitalization, however, was increased in the salmeterol group (2% [35/1,653]) versus the placebo group (less than 1% [16/1,622]; relative risk: 2.1 [95% CI: 1.1, 3.7]).

The data from the SMART trial were not adequate to determine whether concurrent use of ICS or other long-term asthma control therapy mitigated the risk of asthma-related death.

Table 5: Asthma-Related Deaths in the 28-Week Salmeterol Multicenter Asthma Research Trial (SMART)
 | Salmeterol; n (%a) | Placebo; n (%a) | Relative Riskb; (95% Confidence Interval) | Excess Deaths Expressed per 10,000 Subjectsc; (95% Confidence Interval)
Total Populationd
Salmeterol: n = 13,176 | 13 (0.10%) |  | 4.37 (1.25, 15.34) | 8 (3, 13)
Placebo: n = 13,179 |  | 3 (0.02%)
Caucasian
Salmeterol: n = 9,281 | 6 (0.07%) |  | 5.82 (0.70, 48.37) | 6 (1, 10)
Placebo: n = 9,361 |  | 1 (0.01%)
African American
Salmeterol: n = 2,366 | 7 (0.31%) |  | 7.26 (0.89, 58.94) | 27 (8, 46)
Placebo: n = 2,319 |  | 1 (0.04%)
a Life-table 28-week estimate, adjusted according to the subjects’ actual lengths of exposure to study treatment to account for early withdrawal of subjects from the study.
b Relative risk is the ratio of the rate of asthma-related death in the salmeterol group and the rate in the placebo group. The relative risk indicates how many more times likely an asthma-related death occurred in the salmeterol group than in the placebo group in a 28-week treatment period.
c Estimate of the number of additional asthma-related deaths in subjects treated with salmeterol in SMART, assuming 10,000 subjects received salmeterol for a 28-week treatment period. Estimate calculated as the difference between the salmeterol and placebo groups in the rates of asthma-related death multiplied by 10,000.
d The Total Population includes the following ethnic origins listed on the case report form: Caucasian, African American, Hispanic, Asian, and “Other.” In addition, the Total Population includes those subjects whose ethnic origin was not reported. The results for Caucasian and African American subpopulations are shown above. No asthma-related deaths occurred in the Hispanic (salmeterol n = 996, placebo n = 999), Asian (salmeterol n = 173, placebo n = 149), or “Other” (salmeterol n = 230, placebo n = 224) subpopulations. One asthma-related death occurred in the placebo group in the subpopulation whose ethnic origin was not reported (salmeterol n = 130, placebo n = 127).

Figure 2. Cumulative Incidence of Asthma-Related Deaths in the 28-Week Salmeterol Multicenter Asthma Research Trial (SMART), by Duration of Treatment

14.2 Exercise-Induced Bronchospasm

In 2 randomized, single-dose, crossover trials in adolescents and adults with EIB (N = 52), 50 mcg of SEREVENT DISKUS prevented EIB when dosed 30 minutes prior to exercise. For some subjects, this protective effect against EIB was still apparent up to 8.5 hours following a single dose (Table 6).

Table 6. Results of 2 Exercise-Induced Bronchospasm Trials in Adolescents and Adults
 |  | SEREVENT DISKUS; (N = 52) |  | Placebo; (N = 52)
 |  | n | % Total | n | % Total
0.5-Hour postdose exercise challenge | % Fall in FEV1
0.5-Hour postdose exercise challenge | <10% | 31 | 60 | 15 | 29
0.5-Hour postdose exercise challenge | ≥10%, <20% | 11 | 21 | 3 | 6
0.5-Hour postdose exercise challenge | ≥20% | 10 | 19 | 34 | 65
Mean maximal % fall in FEV1 (SE) |  | -11% (1.9) |  | -25% (1.8)
8.5-Hour postdose exercise challenge | % Fall in FEV1
8.5-Hour postdose exercise challenge | <10% | 26 | 50 | 12 | 23
8.5-Hour postdose exercise challenge | ≥10%, <20% | 12 | 23 | 7 | 13
8.5-Hour postdose exercise challenge | ≥20% | 14 | 27 | 33 | 63
Mean maximal % fall in FEV1 (SE) |  | -16% (2.0) |  | -27% (1.5)

In 2 randomized trials in children aged 4 to 11 years with asthma and EIB (N = 50), a single 50-mcg dose of SEREVENT DISKUS prevented EIB when dosed 30 minutes prior to exercise, with protection lasting up to 11.5 hours in repeat testing following this single dose in many subjects.

14.3 Chronic Obstructive Pulmonary Disease

In 2 clinical trials evaluating twice-daily treatment with SEREVENT DISKUS 50 mcg (n = 336) compared with placebo (n = 366) in subjects with chronic bronchitis with airflow limitation, with or without emphysema, improvements in pulmonary function endpoints were greater with salmeterol 50 mcg than with placebo. Treatment with SEREVENT DISKUS did not result in significant improvements in secondary endpoints assessing COPD symptoms in either clinical trial. Both trials were randomized, double-blind, parallel-group trials of 24 weeks’ duration and were identical in design, subject entrance criteria, and overall conduct.

Figure 3 displays the integrated 2-hour postdose FEV1 results from the 2 clinical trials. The percent change in FEV1 refers to the change from baseline, defined as the predose value on Treatment Day 1. To account for subject withdrawals during the trial, Endpoint (last evaluable FEV1) data are provided. Subjects receiving SEREVENT DISKUS 50 mcg had significantly greater improvements in 2-hour postdose FEV1 at Endpoint (216 mL, 20%) compared with placebo (43 mL, 5%). Improvement was apparent on the first day of treatment and maintained throughout the 24 weeks of treatment.

Figure 3. Mean Percent Change from Baseline in Postdose FEV1 Integrated Data from 2 Trials of Subjects with Chronic Bronchitis and Airflow Limitation

Onset of Action and Duration of Effect

The onset of action and duration of effect of SEREVENT DISKUS were evaluated in a subset of subjects (n = 87) from 1 of the 2 clinical trials discussed above. Following the first 50-mcg dose, significant improvement in pulmonary function (mean FEV1 increase of 12% or more and at least 200 mL) occurred at 2 hours. The mean time to peak bronchodilator effect was 4.75 hours. As seen in Figure 4, evidence of bronchodilatation was seen throughout the 12-hour period. Figure 4 also demonstrates that the bronchodilating effect after 12 weeks of treatment was similar to that observed after the first dose. The mean time to peak bronchodilator effect after 12 weeks of treatment was 3.27 hours.

Figure 4. Serial 12-Hour FEV1 on the First Day and at Week 12 of Treatment

16 HOW SUPPLIED/STORAGE AND HANDLING

SEREVENT DISKUS is supplied as a disposable teal green plastic inhaler containing a foil blister strip with 60 blisters. The inhaler is packaged in a plastic-coated, moisture-protective foil pouch (NDC 0173-0521-00).

Store at room temperature between 68°F and 77°F (20°C and 25°C); excursions permitted from 59°F to 86°F (15°C to 30°C) [See USP Controlled Room Temperature]. Store in a dry place away from direct heat or sunlight. Keep out of reach of children.

SEREVENT DISKUS should be stored inside the unopened moisture-protective foil pouch and only removed from the pouch immediately before initial use. Discard SEREVENT DISKUS 6 weeks after opening the foil pouch or when the counter reads “0” (after all blisters have been used), whichever comes first. The inhaler is not reusable. Do not attempt to take the inhaler apart.

17 PATIENT COUNSELING INFORMATION

Advise the patient to read the FDA-approved patient labeling (Medication Guide and Instructions for Use).

Asthma-Related Death

Inform patients that salmeterol when used alone increases the risk of asthma-related death and may increase the risk of asthma-related hospitalization in pediatric and adolescent patients. Inform patients that SEREVENT DISKUS should not be the only therapy for the treatment of asthma and must only be used as additional therapy when ICS do not adequately control asthma symptoms. Inform patients that when SEREVENT DISKUS is added to their treatment regimen they must continue to use their ICS.

Not for Acute Symptoms

Inform patients that SEREVENT DISKUS is not meant to relieve acute asthma symptoms or exacerbations of COPD and extra doses should not be used for that purpose. Advise patients to treat acute symptoms with an inhaled, short-acting beta2-agonist such as albuterol. Provide patients with such medication and instruct them in how it should be used.

Instruct patients to seek medical attention immediately if they experience any of the following:

- Decreasing effectiveness of inhaled, short-acting beta2-agonists
- Need for more inhalations than usual of inhaled, short-acting beta2-agonists
- Significant decrease in lung function as outlined by the physician

Tell patients they should not stop therapy with SEREVENT DISKUS without physician/provider guidance since symptoms may recur after discontinuation.

Not a Substitute for Corticosteroids

Advise all patients with asthma that they must also continue regular maintenance treatment with an ICS if they are taking SEREVENT DISKUS.

SEREVENT DISKUS should not be used as a substitute for oral or inhaled corticosteroids. The dosage of these medications should not be changed and they should not be stopped without consulting the physician, even if the patient feels better after initiating treatment with SEREVENT DISKUS.

Do Not Use Additional Long-acting Beta2-agonists

Instruct patients not to use other LABA.

Immediate Hypersensitivity Reactions

Advise patients that immediate hypersensitivity reactions (e.g., urticaria, angioedema, rash, bronchospasm, hypotension), including anaphylaxis, may occur after administration of SEREVENT DISKUS. Patients should discontinue SEREVENT DISKUS if such reactions occur. There have been reports of anaphylactic reactions in patients with severe milk protein allergy after inhalation of powder products containing lactose; therefore, patients with severe milk protein allergy should not take SEREVENT DISKUS.

Risks Associated with Beta-agonist Therapy

Inform patients of adverse effects associated with beta2-agonists, such as palpitations, chest pain, rapid heart rate, tremor, or nervousness.

Treatment of Exercise-Induced Bronchospasm

Patients using SEREVENT DISKUS for the treatment of EIB should not use additional doses for 12 hours. Patients who are receiving SEREVENT DISKUS twice daily should not use additional SEREVENT for prevention of EIB.

Trademarks are owned by or licensed to the GSK group of companies.

GlaxoSmithKline

Durham, NC 27701

©2022 GSK group of companies or its licensor.

SRD:17PI

MEDICATION GUIDE

SEREVENT DISKUS (SER uh vent DISK us)

(salmeterol xinafoate inhalation powder)

for oral inhalation use

What is the most important information I should know about SEREVENT DISKUS?

SEREVENT DISKUS can cause serious side effects, including:

- People with asthma who take long-acting beta2-adrenergic agonist (LABA) medicines, such as salmeterol (the medicine in SEREVENT DISKUS), have an increased risk of death from asthma problems if they use SEREVENT DISKUS without also using a medicine called an inhaled corticosteroid (ICS).
- Call your healthcare provider if breathing problems worsen over time while using SEREVENT DISKUS. You may need different treatment.
- Get emergency medical care if:
- your breathing problems worsen quickly.
- you use your rescue inhaler, but it does not relieve your breathing problems.
- Do not use SEREVENT DISKUS as your only asthma medicine. SEREVENT DISKUS must only be used with an ICS.
- SEREVENT DISKUS should be used only if your healthcare provider decides that your asthma is not well controlled with an ICS.
- Children and adolescents who take LABA medicines as their only asthma medicine may have an increased risk of being hospitalized for asthma problems.

What is SEREVENT DISKUS?

- SEREVENT DISKUS is a prescription inhaled LABA medicine. LABA medicines such as salmeterol help the muscles around the airways in your lungs stay relaxed to prevent symptoms, such as wheezing, cough, chest tightness, and shortness of breath. These symptoms can happen when the muscles around the airways tighten. This makes it hard to breathe.
- SEREVENT DISKUS is not used to relieve sudden breathing problems and will not replace a rescue inhaler.
- It is not known if SEREVENT DISKUS is safe and effective in children younger than 4 years.
- SEREVENT DISKUS is used for asthma, exercise-induced bronchospasm (EIB), and chronic obstructive pulmonary disease (COPD) as follows:
Asthma:
- SEREVENT DISKUS is a prescription medicine used to control symptoms of asthma and to prevent symptoms such as wheezing in adults and children aged 4 years and older.
- SEREVENT DISKUS contains salmeterol. LABA medicines such as salmeterol when used alone increase the risk of death from asthma problems.
- SEREVENT DISKUS is not for adults and children with asthma who are well controlled with an asthma control medicine, such as a low to medium dose of an ICS medicine.
Exercise-Induced Bronchospasm (EIB):
- SEREVENT DISKUS is used to prevent wheezing caused by exercise in adults and children aged 4 years and older.
- If you only have EIB, your healthcare provider may only prescribe SEREVENT DISKUS for your condition.
- If you have EIB and asthma, your healthcare provider should also prescribe an ICS.
Chronic Obstructive Pulmonary Disease (COPD):
- COPD is a chronic lung disease that includes chronic bronchitis, emphysema, or both.
- SEREVENT DISKUS is a prescription medicine used long term as 1 inhalation 2 times each day to improve symptoms of COPD for better breathing.

Do not use SEREVENT DISKUS:

- to treat your asthma without an ICS.
- to treat sudden, severe symptoms of asthma or COPD.
- if you have a severe allergy to milk proteins. Ask your healthcare provider if you are not sure.
- if you are allergic to salmeterol xinafoate or any of the ingredients in SEREVENT DISKUS. See the end of this Medication Guide for a complete list of ingredients in SEREVENT DISKUS.

Before using SEREVENT DISKUS, tell your healthcare provider about all of your medical conditions, including if you:

- have heart problems.
- have high blood pressure.
- have seizures.
- have thyroid problems.
- have diabetes.
- have liver problems.
- are allergic to milk proteins.
- are pregnant or plan to become pregnant. It is not known if the medicine salmeterol in SEREVENT DISKUS may harm your unborn baby.
- are breastfeeding or plan to breastfeed. It is not known if the medicine in SEREVENT DISKUS passes into your breast milk and if it can harm your baby.

Tell your healthcare provider about all the medicines you take, including prescription and over-the-counter medicines, vitamins, and herbal supplements. SEREVENT DISKUS and certain other medicines may interact with each other. This may cause serious side effects. Especially tell your healthcare provider if you take antifungal or anti-HIV medicines.

Know the medicines you take. Keep a list of them to show your healthcare provider and pharmacist when you get a new medicine.

How should I use SEREVENT DISKUS?

Read the step-by-step instructions for using SEREVENT DISKUS at the end of this Medication Guide.

- Do not use SEREVENT DISKUS unless your healthcare provider has taught you how to use the inhaler and you understand how to use it correctly.
- Children should use SEREVENT DISKUS with an adult’s help, as instructed by the child’s healthcare provider.
- Use SEREVENT DISKUS exactly as your healthcare provider tells you to use it. Do not use SEREVENT DISKUS more often than prescribed.
- For asthma and COPD, the usual dose is 1 inhalation of SEREVENT DISKUS 2 times each day. Use SEREVENT DISKUS at the same time each day, about 12 hours apart.
- For preventing exercise-induced bronchospasm, the usual dose is 1 inhalation at least 30 minutes before exercise. Do not use SEREVENT DISKUS more often than every 12 hours. Do not use extra SEREVENT DISKUS before exercise if you already use it 2 times each day.
- If you miss a dose of SEREVENT DISKUS, just skip that dose. Take your next dose at your usual time. Do not take 2 doses at 1 time.
- If you take too much SEREVENT DISKUS, call your healthcare provider or go to the nearest hospital emergency room right away if you have any unusual symptoms, such as worsening shortness of breath, chest pain, increased heart rate, or shakiness.
- Do not use other medicines that contain a LABA for any reason. Ask your healthcare provider or pharmacist if any of your other medicines are LABA medicines.
- Do not stop using SEREVENT DISKUS unless told to do so by your healthcare provider because your symptoms might get worse. Your healthcare provider will change your medicines as needed.
- SEREVENT DISKUS does not relieve sudden breathing problems. Always have a rescue inhaler with you to treat sudden symptoms. If you do not have a rescue inhaler, call your healthcare provider to have one prescribed for you.
- Call your healthcare provider or get medical care right away if:
- your breathing problems get worse.
- you need to use your rescue inhaler more often than usual.
- your rescue inhaler does not work as well to relieve your symptoms.
- you need to use 4 or more inhalations of your rescue inhaler in 24 hours for 2 or more days in a row.
- you use 1 whole canister of your rescue inhaler in 8 weeks.
- your peak flow meter results decrease. Your healthcare provider will tell you the numbers that are right for you.
- you have asthma and your symptoms do not improve after using SEREVENT DISKUS regularly for 1 week.

What are the possible side effects of SEREVENT DISKUS?

SEREVENT DISKUS can cause serious side effects, including:

- See “What is the most important information I should know about SEREVENT DISKUS?”
- sudden breathing problems immediately after inhaling your medicine. If you have sudden breathing problems immediately after inhaling your medicine, stop using SEREVENT DISKUS and call your healthcare provider right away.
- effects on heart.

ο increased blood pressure ο chest pain

ο a fast or irregular heartbeat, awareness of heartbeat

- effects on nervous system.

ο tremor ο nervousness

- serious allergic reactions. Call your healthcare provider or get emergency medical care if you get any of the following symptoms of a serious allergic reaction:

ο rash ο swelling of your face, mouth, and tongue

ο hives ο breathing problems

- changes in laboratory blood levels, including high levels of blood sugar (hyperglycemia) and low levels of potassium (hypokalemia)

Common side effects of SEREVENT DISKUS include:

Asthma:

• headache • nasal congestion • bronchitis

• throat irritation • runny nose • flu

COPD:

• headache • musculoskeletal pain • throat irritation

• cough • respiratory infection

These are not all the possible side effects of SEREVENT DISKUS.

Call your doctor for medical advice about side effects. You may report side effects to FDA at 1-800-FDA-1088.

How should I store SEREVENT DISKUS?

- Store SEREVENT DISKUS at room temperature between 68°F and 77°F (20°C and 25°C).
- Store SEREVENT DISKUS in a dry place away from heat and sunlight.
- Store SEREVENT DISKUS in the unopened foil pouch and only open when ready for use.
- Safely throw away SEREVENT DISKUS in the trash 6 weeks after you open the foil pouch or when the counter reads “0”, whichever comes first. Write the date you open the pouch on the label on the inhaler.

Keep SEREVENT DISKUS and all medicines out of the reach of children.

General information about the safe and effective use of SEREVENT DISKUS.

Medicines are sometimes prescribed for purposes other than those listed in a Medication Guide. Do not use SEREVENT DISKUS for a condition for which it was not prescribed. Do not give SEREVENT DISKUS to other people, even if they have the same symptoms that you have. It may harm them.

You can ask your healthcare provider or pharmacist for information about SEREVENT DISKUS that was written for health professionals.

What are the ingredients in SEREVENT DISKUS?

Active ingredient: salmeterol xinafoate

Inactive ingredients: lactose monohydrate (contains milk proteins)

For more information about SEREVENT DISKUS, call 1-888-825-5249.

Trademarks are owned by or licensed to the GSK group of companies.

GlaxoSmithKline, Durham, NC 27701

©2022 GSK group of companies or its licensor.

SRD:8MG

This Medication Guide has been approved by the U.S. Food and Drug Administration Revised: October 2022

INSTRUCTIONS FOR USE

SEREVENT DISKUS (SER uh vent DISK us)

(salmeterol xinafoate inhalation powder)

for oral inhalation use

Read this Instructions for Use before you start using SEREVENT DISKUS and each time you get a refill. There may be new information. This information does not take the place of talking to your healthcare provider about your medical condition or treatment.

Your SEREVENT DISKUS inhaler

Figure A

Important information about your SEREVENT DISKUS inhaler:

- SEREVENT DISKUS is for oral inhalation use only.
- Take SEREVENT DISKUS out of the foil pouch just before you use it for the first time. Safely throw away the pouch. The DISKUS will be in the closed position.
- Write the date you opened the foil pouch in the first blank line on the label. See Figure A.
- Write the “use by” date in the second blank line on the label. See Figure A. That date is 6 weeks after the date you wrote in the first line.
- The counter should read 60.

How to use your SEREVENT DISKUS inhaler

Follow these steps every time you use SEREVENT DISKUS.

Step 1. Open your SEREVENT DISKUS.

- Hold the DISKUS in your left hand and place the thumb of your right hand in the thumb grip. Push the thumb grip away from you as far as it will go until the mouthpiece shows and snaps into place. See Figure B.

Figure B

Step 2. Slide the lever until you hear it click.

- Hold the DISKUS in a level, flat position with the mouthpiece towards you. Slide the lever away from the mouthpiece as far as it will go until it clicks. See Figure C.

Figure C

- The number on the counter will count down by 1. The DISKUS is now ready to use.

Follow the instructions below so you will not accidentally waste a dose:

- Do not close the DISKUS.
- Do not tilt the DISKUS.
- Do not move the lever on the DISKUS.

Step 3. Inhale your medicine.

- Before you breathe in your dose from the DISKUS, breathe out (exhale) as long as you can while you hold the DISKUS level and away from your mouth. See Figure D. Do not breathe into the mouthpiece.

Figure D

- Put the mouthpiece to your lips. See Figure E. Breathe in quickly and deeply through the DISKUS. Do not breathe in through your nose.

Figure E

- Remove the DISKUS from your mouth and hold your breath for about 10 seconds, or for as long as is comfortable for you.
- Breathe out slowly as long as you can. See Figure D.
- The DISKUS delivers your dose of medicine as a very fine powder that you may or may not taste or feel. Do not take an extra dose from the DISKUS even if you do not taste or feel the medicine.

Step 4. Close the DISKUS.

- Place your thumb in the thumb grip and slide it back towards you as far as it will go. See Figure F. Make sure the DISKUS clicks shut and you cannot see the mouthpiece.

Figure F

- The DISKUS is now ready for you to take your next scheduled dose in about 12 hours. When you are ready to take your next dose, repeat Steps 1 through 4.

When should you get a refill?

The counter on top of the DISKUS shows you how many doses are left. After you have taken 55 doses, the numbers 5 to 0 will show in red. See Figure G. These numbers warn you there are only a few doses left and are a reminder to get a refill.

Figure G

For correct use of the DISKUS, remember:

- Always use the DISKUS in a level, flat position.
- Make sure the lever firmly clicks into place.
- Hold your breath for about 10 seconds after inhaling. Then breathe out fully.
- Do not take an extra dose, even if you did not taste or feel the powder.
- Do not take the DISKUS apart.
- Do not wash the DISKUS.
- Always keep the DISKUS in a dry place.
- Do not use the DISKUS with a spacer device.

For more information about SEREVENT DISKUS or how to use your inhaler, call 1-888-825-5249.

Trademarks are owned by or licensed to the GSK group of companies.

GlaxoSmithKline, Durham, NC 27701

©2022 GSK group of companies or its licensor.

SRD:4IFU

This Instructions for Use has been approved by the U.S. Food and Drug Administration Revised: October 2022

PACKAGE LABEL

PRINCIPAL DISPLAY PANEL

NDC 0173-0521-00

Serevent Diskus

(salmeterol xinafoate inhalation powder)

50 mcg

FOR ORAL INHALATION ONLY

Each blister contains 50 mcg of salmeterol base with lactose monohydrate.

Federal Law requires the dispensing of SEREVENT DISKUS with the Medication Guide inside the carton.

See prescribing information for dosing information.

Rx only

GSK

1 DISKUS Inhalation Device Containing 1 Foil Strip of 60 Blisters

Made in Singapore

©2022 GSK group of companies or its licensor.

62000000084267 Rev. 12/22